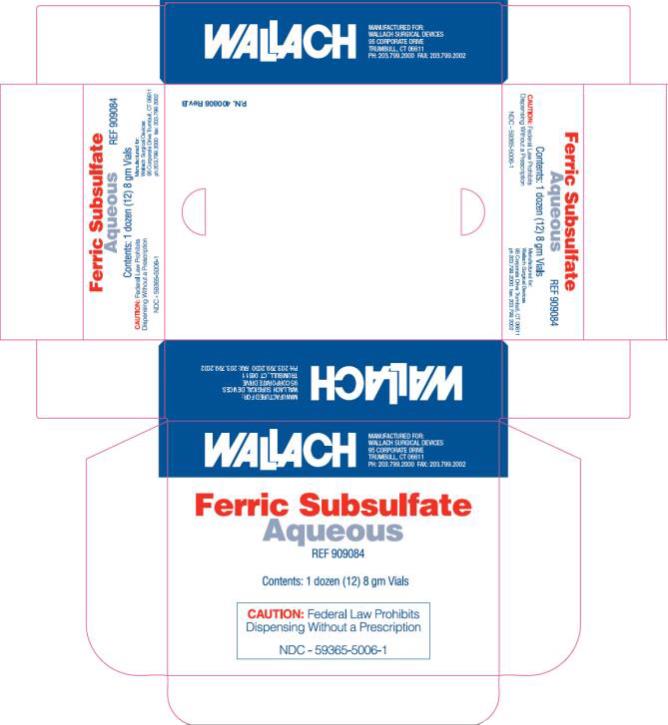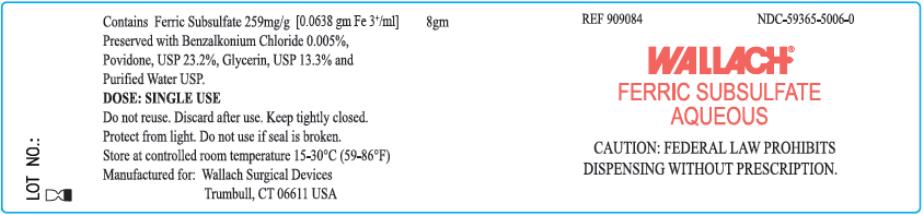 DRUG LABEL: Ferric Subsulfate
NDC: 59365-5006 | Form: SOLUTION
Manufacturer: CooperSurgical, Inc.
Category: prescription | Type: HUMAN PRESCRIPTION DRUG LABEL
Date: 20160525

ACTIVE INGREDIENTS: FERRIC SUBSULFATE 259 mg/1 g
INACTIVE INGREDIENTS: BENZALKONIUM CHLORIDE; POVIDONE; GLYCERIN; WATER

Ferric Subsulfate Aqueous

DESCRIPTION

Ferric Subsulfate, Aqueous; 8gm single-use glass vials.

CONTENTS

Ferric subsulfate 259mg/g [0.0638gm Fe ^3+/ml]. Preserved with benzalkonium chloride 0.005%. Povidone USP 23.2%. Glycerin USP 13.3%. Purified Water USP.

INDICATIONS AND USAGE

Ferric Subsulfate, Aqueous, is a stypic agent used for achieving local hemostasis. In punch biopsies of the full dermis, the time to achieve hemostasis is typically less than 20 seconds.^1 One method of applying ferric subsulfate solution for dermal use consists of the physician placing fingers at the opposite edge of the wound and stretching the skin. The wound is then wiped with gauze, the ferric subsulfate solution applied, and the tension maintained for approximately 15 seconds.^2

WARNINGS

For External Use Only. Should inadvertent eye contact occur, the eye(s) should be washed immediately with large amounts of water or normal saline, occasionally lifting the upper and lower lids until no evidence of solution remains (approximately 15-20 minutes).

PRECAUTIONS

As with all iron solutions applied to dermal surfaces denuded of epithelium or to mucous membranes topical application of Ferric Subsulfate Aqueous (ferric subsulfate) may result in hyperpigmentation (“tattooing”).^3,4 Microscopically, this hyperpigmentation may be observed as ferrugination of collagen fibers and fibrin.^5 In one study of uterine cervical tissue, ferric subsulfate solution penetrated denuded mucosa and produced coagulation necrosis to a maximum depth of 0.6mm.^6 In an in vitro study, ferric subsulfate solution produced a radiopacity with a density intermediate between that of water/tissue and calcium.^7

Should a re-biopsy of the same lesion be required, pathologists and other physicians involved in the care of the patient should be aware of the previous use of ferric subsulfate solution. Previous use of ferric subsulfate solution may result in a histologic artifact upon re-biopsy of heavy pigmentation, similar to hemosiderin, together with shrinkage and discoloration of collagen bundles.^8,9 Similarly, previous use of ferric subsulfate solution may result in a radiographic artifact.

CAUTION

Federal law (USA) prohibits dispensing without a prescription.

STORAGE

Keep tightly closed and protect from light. DO NOT use if seal is broken. Store at room temperature 59°-86°F (15°-30° C).

DISPOSAL

Opened containers with unused portions of product and applicator swabs containing residual product should be placed in a suitable, dry container for later disposal according to local hazardous waste practices. Waste containing Ferric Subsulfate Aqueous should not be subjected to any thermal process whether intended for destruction or recycling purposes.

REFERENCES

- Armstrong RB, Nichols J. Pachance J. Punch biopsy wounds treated with Monsel’s solution or a collagen matrix. A comparison of healing. Arch. Dermatol 1986;122:546-549.
- Baden HP, Rapid hemostasis with Monsel’s solution (letter). Arch Dermatol 1984; 120:708.
- Demis DJ, Clinical dermatology, Hagerstown MD: Harper & Row, 1986; pp. 11-4:1-11-4:5.
- Camisa C., Roberts W. Monsel solution tattooing (letter). J Am Acad Dermatol 1983;8:753-754.
- Amazon K, Robinson MJ, Rywlin AM. Ferrugination caused by Monsel’s solution. Clinical observations and experimentation. Am J Dermatopathol 1980;2:197-205.
- Davis JR, Steinbronn KK, Graham AR, Dawson BV. Effects of Monsel’s solution in uterine cervix, AM J Clin Pathol 1984;82:332-335.
- Horn MS, Circeo RB, Hassan C. Radiographic artifacts produced by silver nitrate and Monsel’s solution (letter). J Am Acad Dernatol 1983;8:560-562.
- Olmstead PM, Lund HZ, Leonard DD. Monsel’s solution: a histologic nuisance. J Am Acad Dermatol 1980;3:492-498.
- Wood C, Severin GL. Unusual histiocytic reaction to Monsel’s solution. Am J Dermatopathol 1980;2:261-264.

PRINCIPAL DISPLAY PANEL

Ferric Subsulfate
Aqueous
Contents: 1 dozen (12) 8gm Vials

PRINCIPAL DISPLAY PANEL

8gm NDC 59365-5006-0
FERRIC SUBSULFATE
AQUEOUS